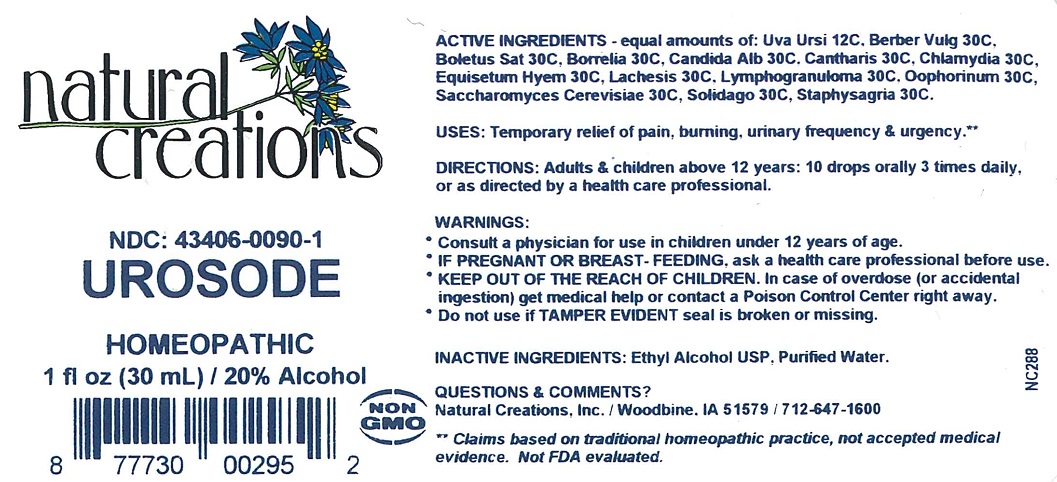 DRUG LABEL: Urosode
NDC: 43406-0090 | Form: LIQUID
Manufacturer: Natural Creations, Inc
Category: homeopathic | Type: HUMAN OTC DRUG LABEL
Date: 20181221

ACTIVE INGREDIENTS: ARCTOSTAPHYLOS UVA-URSI LEAF 12 [hp_C]/1 mL; BOLETUS SATANAS FRUITING BODY 30 [hp_C]/1 mL; BERBERIS VULGARIS ROOT BARK 30 [hp_C]/1 mL; BORRELIA BURGDORFERI 30 [hp_C]/1 mL; CANDIDA ALBICANS 30 [hp_C]/1 mL; CHLAMYDIA TRACHOMATIS 30 [hp_C]/1 mL; EQUISETUM HYEMALE WHOLE 30 [hp_C]/1 mL; LACHESIS MUTA VENOM 30 [hp_C]/1 mL; SUS SCROFA OVARY 30 [hp_C]/1 mL; SACCHAROMYCES CEREVISIAE 30 [hp_C]/1 mL; SOLIDAGO VIRGAUREA FLOWERING TOP 30 [hp_C]/1 mL; DELPHINIUM STAPHISAGRIA SEED 30 [hp_C]/1 mL
INACTIVE INGREDIENTS: ALCOHOL; WATER

Urosode

ACTIVE INGREDIENT

ACTIVE INGREDIENTS - equal amounts of: Uva Ursi 12C, Berber Vulg 30C, Boletus Sat 30C, Borrelia 30C, Candida Alb 30C, Cantharis 30C, Chlamydia 30C, Equisetum Hyem 30C, Lachesis 30C, Lymphogranuloma 30C, Oophorinum 30C, Saccharomyces Cerevisiae 30C, Solidago 30C, Staphysagria 30C.

INDICATIONS AND USAGE

USES: Temporary relief of pain, burning, urinary frequency & urgency.**

PURPOSE

USES: Temporary relief of pain, burning, urinary frequency & urgency.**

DOSAGE AND ADMINISTRATION

DIRECTIONS: Adults & children above 12 years: 10 drops orally 3 times daily, or as directed by a health care professional.

KEEP OUT OF REACH OF CHILDREN

KEEP OUT OF THE REACH OF CHILDREN. In case of overdose (or accidental ingestion) get medical help or contact a Poison Control Center right away.

WARNINGS:

- Consult a physician for use in children under 12 years of age.
- IF PREGNANT OR BREAST-FEEDING, ask a health care professional before use.
- KEEP OUT OF THE REACH OF CHILDREN. In case of overdose (or accidental ingestion) get medical help or contact a Poison Control Center right away.
- Do not use if TAMPER EVIDENT seal is broken or missing.

INACTIVE INGREDIENTS: Ethyl Alcohol USP, Purified Water.

QUESTIONS & COMMENTS?

Natural Creations, Inc. / Woodbine, IA 51579 / 712-647-1600

REFERENCES

**Claims based on traditional homeopathic practice, not accepted medical evidence. Not FDA evaluated.

PACKAGE LABEL

NDC:43406-0090-1

Urosode

HOMEOPATHIC

1 fl oz (30mL) / 20% Alcohol